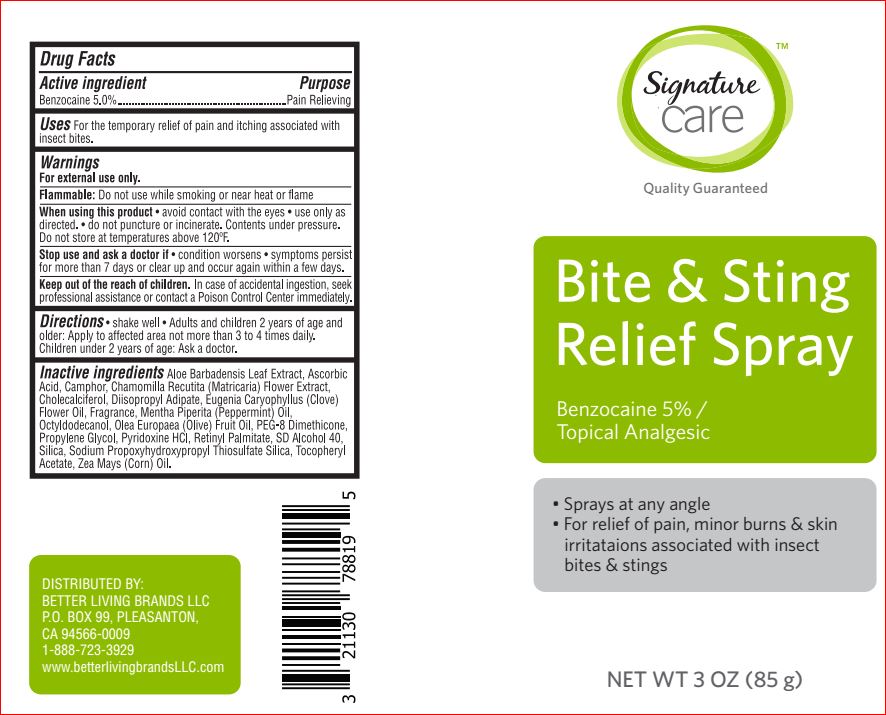 DRUG LABEL: Bite and Sting Relief
NDC: 21130-337 | Form: SPRAY
Manufacturer: Better Living
Category: otc | Type: HUMAN OTC DRUG LABEL
Date: 20180118

ACTIVE INGREDIENTS: Benzocaine 5 g/100 g
INACTIVE INGREDIENTS: ALOE VERA LEAF; Ascorbic Acid; CAMPHOR (SYNTHETIC); CHAMOMILE; Cholecalciferol; Diisopropyl Adipate; CLOVE OIL; PEPPERMINT OIL; Octyldodecanol; OLIVE OIL; PEG-8 Dimethicone; Propylene Glycol; PYRIDOXINE HYDROCHLORIDE; VITAMIN A PALMITATE; ALCOHOL; SILICON DIOXIDE; Sodium Propoxyhydroxypropyl Thiosulfate Silica; .ALPHA.-TOCOPHEROL ACETATE; CORN OIL

Drug Facts

Active ingredient Purpose
Benzocaine 5%..........................................................Topical anesthetic

Uses

For the temporary relief of pain and itching associated with insect bites.

Warnings
For external use only.

Flammable: Do not use while smoking or near heat or flame
When using this product • use only as directed • avoid contact with eyes

Do not puncture or incenerate. Contents under pressure. Do not store at temperature above 120F
Stop use and ask a doctor if • condition worsens • symptoms persist for more than 7 days or clear up and occur again within
a few days.

Keep out of reach of children. If swallowed, get medical help or contact a Poison Control Center immediately

Directions
Shake well. Adults and children 2 years of age and older: Apply to affected area not more than 3 to 4 times daily. Children under 2 years of
age: consult a doctor.

Inactive ingredients

Aloe Barbadensis Leaf Extract
Ascorbic Acid
Camphor
Chamomilla Recutita (Matricaria) Flower Extract
Cholecalciferol
Diisopropyl Adipate
Eugenia Caryophyllus (Clove) Flower Oil
Fragrance
Mentha Piperita (Peppermint) Oil
Octyldodecanol
Olea Europaea (Olive) Fruit Oil
PEG-8 Dimethicone
Propylene Glycol
Pyridoxine HCl
Retinyl Palmitate
SD Alcohol 40
Silica
Sodium Propoxyhydroxypropyl Thiosulfate Silica
Tocopheryl Acetate
Zea Mays (Corn) Oil